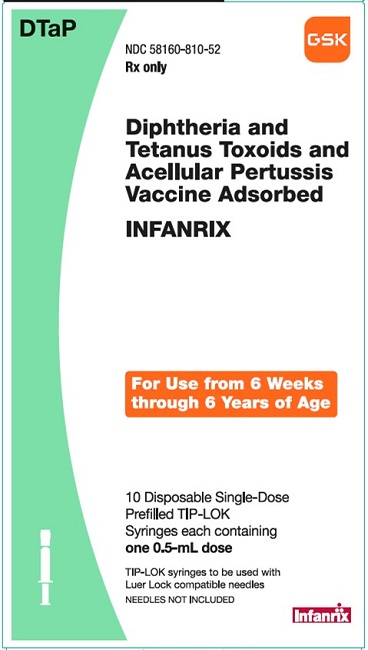 DRUG LABEL: INFANRIX
NDC: 58160-810 | Form: SUSPENSION
Manufacturer: GlaxoSmithKline Biologicals SA
Category: other | Type: VACCINE LABEL
Date: 20241202

ACTIVE INGREDIENTS: CLOSTRIDIUM TETANI TOXOID ANTIGEN (FORMALDEHYDE INACTIVATED) 10 [iU]/0.5 mL; CORYNEBACTERIUM DIPHTHERIAE TOXOID ANTIGEN (FORMALDEHYDE INACTIVATED) 25 [iU]/0.5 mL; BORDETELLA PERTUSSIS TOXOID ANTIGEN (FORMALDEHYDE, GLUTARALDEHYDE INACTIVATED) 25 ug/0.5 mL; BORDETELLA PERTUSSIS FILAMENTOUS HEMAGGLUTININ ANTIGEN (FORMALDEHYDE INACTIVATED) 25 ug/0.5 mL; BORDETELLA PERTUSSIS PERTACTIN ANTIGEN (FORMALDEHYDE INACTIVATED) 8 ug/0.5 mL
INACTIVE INGREDIENTS: ALUMINUM HYDROXIDE; FORMALDEHYDE; SODIUM CHLORIDE; POLYSORBATE 80

HIGHLIGHTS OF PRESCRIBING INFORMATION

These highlights do not include all the information needed to use INFANRIX safely and effectively. See full prescribing information for INFANRIX.
INFANRIX (Diphtheria and Tetanus Toxoids and Acellular Pertussis Vaccine Adsorbed) Suspension for Intramuscular Injection
Initial U.S. Approval: 1997

1 INDICATIONS AND USAGE

INFANRIX is a vaccine indicated for active immunization against diphtheria, tetanus, and pertussis as a 5-dose series in infants and children aged 6 weeks through 6 years (prior to the seventh birthday). (1)

2 DOSAGE AND ADMINISTRATION

A 0.5-mL intramuscular injection given as a 5-dose series: (2.2)

- One dose each at 2, 4, and 6 months of age.
- One booster dose at 15 to 20 months of age and another booster dose at 4 to 6 years of age.

3 DOSAGE FORMS AND STRENGTHS

Single-dose, prefilled syringes containing a 0.5-mL suspension for injection. (3)

4 CONTRAINDICATIONS

- Severe allergic reaction (e.g., anaphylaxis) after a previous dose of any diphtheria toxoid-, tetanus toxoid-, or pertussis-containing vaccine, or to any component of INFANRIX. (4.1)
- Encephalopathy within 7 days of administration of a previous pertussis-containing vaccine. (4.2)
- Progressive neurologic disorders. (4.3)

5 WARNINGS AND PRECAUTIONS

- If Guillain-Barré syndrome occurs within 6 weeks of receipt of a prior vaccine containing tetanus toxoid, the decision to give INFANRIX should be based on potential benefits and risks. (5.1)
- Syncope (fainting) can occur in association with administration of injectable vaccines, including INFANRIX. Procedures should be in place to avoid falling injury and to restore cerebral perfusion following syncope. (5.2)
- If temperature ≥105°F, collapse or shock-like state, or persistent, inconsolable crying lasting ≥3 hours have occurred within 48 hours after receipt of a pertussis-containing vaccine, or if seizures have occurred within 3 days after receipt of a pertussis-containing vaccine, the decision to give INFANRIX should be based on potential benefits and risks. (5.3)
- For children at higher risk for seizures, an antipyretic may be administered at the time of vaccination with INFANRIX. (5.4)
- Apnea following intramuscular vaccination has been observed in some infants born prematurely. Decisions about when to administer an intramuscular vaccine, including INFANRIX, to infants born prematurely should be based on consideration of the individual infant’s medical status, and the potential benefits and possible risks of vaccination. (5.5)

6 ADVERSE REACTIONS

Rates of injection site reactions (pain, redness, swelling) ranged from 10% to 53%, depending on reaction and dose number, and were highest following Doses 4 and 5. Fever was common (20% to 30%) following Doses 1-3. Other common solicited adverse reactions were drowsiness, irritability/fussiness, and loss of appetite, reported in approximately 15% to 60% of subjects, depending on reaction and dose number. (6.1)

To report SUSPECTED ADVERSE REACTIONS, contact GlaxoSmithKline at 1-888-825-5249 or VAERS at 1-800-822-7967 or www.vaers.hhs.gov.

7 DRUG INTERACTIONS

Do not mix INFANRIX with any other vaccine in the same syringe. (7.1)

FULL PRESCRIBING INFORMATION

1 INDICATIONS AND USAGE

INFANRIX is indicated for active immunization against diphtheria, tetanus, and pertussis as a 5-dose series in infants and children aged 6 weeks through 6 years (prior to the seventh birthday).

2 DOSAGE AND ADMINISTRATION

2.1 Preparation for Administration

Shake vigorously to obtain a homogeneous, turbid, white suspension. Do not use if resuspension does not occur with vigorous shaking. Parenteral drug products should be inspected visually for particulate matter and discoloration prior to administration, whenever solution and container permit. If either of these conditions exists, the vaccine should not be administered.

Attach a sterile needle and administer intramuscularly.

Do not administer this product intravenously, intradermally, or subcutaneously.

2.2 Dose and Schedule

A 0.5-mL dose of INFANRIX is approved for intramuscular administration in infants and children aged 6 weeks through 6 years (prior to the seventh birthday) as a 5-dose series. The series consists of a primary immunization course of 3 doses administered at 2, 4, and 6 months of age (at intervals of 4 to 8 weeks), followed by 2 booster doses, administered at 15 to 20 months of age and at 4 to 6 years of age. The first dose may be given as early as 6 weeks of age.

The preferred administration site is the anterolateral aspect of the thigh for most infants aged younger than 12 months and the deltoid muscle of the upper arm for most children aged 12 months through 6 years.

2.3 Use of INFANRIX with Other DTaP Vaccines

Sufficient data are not available on the safety and effectiveness of interchanging INFANRIX and Diphtheria and Tetanus Toxoids and Acellular Pertussis (DTaP) vaccines from different manufacturers for successive doses of the DTaP vaccination series. Because the pertussis antigen components of INFANRIX and PEDIARIX [Diphtheria and Tetanus Toxoids and Acellular Pertussis Adsorbed, Hepatitis B (Recombinant) and Inactivated Poliovirus Vaccine] are the same, INFANRIX may be used to complete a DTaP vaccination series initiated with PEDIARIX.

2.4 Additional Dosing Information

If any recommended dose of pertussis vaccine cannot be given [see Contraindications (4.2, 4.3), Warnings and Precautions (5.3)], Diphtheria and Tetanus Toxoids Adsorbed (DT) For Pediatric Use should be given according to its prescribing information.

4 CONTRAINDICATIONS

4.1 Hypersensitivity

Severe allergic reaction (e.g., anaphylaxis) after a previous dose of any diphtheria toxoid-, tetanus toxoid-, or pertussis-containing vaccine, or to any component of INFANRIX is a contraindication [see Description (11)]. Because of the uncertainty as to which component of the vaccine might be responsible, no further vaccination with any of these components should be given. Alternatively, such individuals may be referred to an allergist for evaluation if immunization with any of these components is being considered.

4.2 Encephalopathy

Encephalopathy (e.g., coma, decreased level of consciousness, prolonged seizures) within 7 days of administration of a previous dose of a pertussis-containing vaccine that is not attributable to another identifiable cause is a contraindication to administration of any pertussis-containing vaccine, including INFANRIX.

4.3 Progressive Neurologic Disorder

Progressive neurologic disorder, including infantile spasms, uncontrolled epilepsy, or progressive encephalopathy, is a contraindication to administration of any pertussis-containing vaccine, including INFANRIX. Pertussis vaccine should not be administered to individuals with these conditions until a treatment regimen has been established and the condition has stabilized.

5 WARNINGS AND PRECAUTIONS

5.1 Guillain-Barré Syndrome

If Guillain-Barré syndrome occurs within 6 weeks of receipt of a prior vaccine containing tetanus toxoid, the decision to give any tetanus toxoid-containing vaccine, including INFANRIX, should be based on careful consideration of the potential benefits and possible risks. When a decision is made to withhold tetanus toxoid, other available vaccines should be given, as indicated.

5.2 Syncope

Syncope (fainting) can occur in association with administration of injectable vaccines, including INFANRIX. Syncope can be accompanied by transient neurological signs such as visual disturbance, paresthesia, and tonic-clonic limb movements. Procedures should be in place to avoid falling injury and to restore cerebral perfusion following syncope.

5.3 Adverse Reactions following Prior Pertussis Vaccination

If any of the following reactions occur in temporal relation to receipt of a pertussis-containing vaccine, the decision to give any pertussis-containing vaccine, including INFANRIX, should be based on careful consideration of the potential benefits and possible risks:

- Temperature of ≥40.5oC (105oF) within 48 hours not due to another identifiable cause;
- Collapse or shock-like state (hypotonic-hyporesponsive episode) within 48 hours;
- Persistent, inconsolable crying lasting ≥3 hours, occurring within 48 hours;
- Seizures with or without fever occurring within 3 days.

5.4 Children at Risk for Seizures

For children at higher risk for seizures than the general population, an appropriate antipyretic may be administered at the time of vaccination with a pertussis-containing vaccine, including INFANRIX, and for the ensuing 24 hours to reduce the possibility of post-vaccination fever.

5.5 Apnea in Premature Infants

Apnea following intramuscular vaccination has been observed in some infants born prematurely. Decisions about when to administer an intramuscular vaccine, including INFANRIX, to infants born prematurely should be based on consideration of the individual infant’s medical status and the potential benefits and possible risks of vaccination.

5.6 Preventing and Managing Allergic Vaccine Reactions

Prior to administration, the healthcare provider should review the patient’s immunization history for possible vaccine hypersensitivity. Epinephrine and other appropriate agents used for the control of immediate allergic reactions must be immediately available should an acute anaphylactic reaction occur.

6 ADVERSE REACTIONS

6.1 Clinical Trials Experience

Because clinical trials are conducted under widely varying conditions, adverse reaction rates observed in the clinical trials of a vaccine cannot be directly compared with rates in the clinical trials of another vaccine and may not reflect the rates observed in practice.

Approximately 95,000 doses of INFANRIX have been administered in clinical studies. In these studies, 29,243 infants have received INFANRIX in primary series studies: 6,081 children have received a fourth consecutive dose of INFANRIX, 1,764 children have received a fifth consecutive dose of INFANRIX, and 559 children have received a dose of INFANRIX following 3 doses of PEDIARIX.

Solicited Adverse Reactions

In a U.S. study, 335 infants received INFANRIX, ENGERIX-B [Hepatitis B Vaccine (Recombinant)], inactivated poliovirus vaccine (IPV, Sanofi Pasteur SA), Haemophilus b (Hib) conjugate vaccine (Wyeth Pharmaceuticals Inc.; no longer licensed in the United States), and pneumococcal 7-valent conjugate (PCV7) vaccine (Wyeth Pharmaceuticals Inc.) concomitantly at separate sites. All vaccines were administered at 2, 4, and 6 months of age. Data on solicited local reactions and general adverse reactions were collected by parents using standardized diary cards for 4 consecutive days following each vaccine dose (i.e., day of vaccination and the next 3 days) (Table 1). Among subjects, 69% were White, 16% were Hispanic, 8% were Black, 4% were Asian, and 2% were of other racial/ethnic groups.

Table 1. Solicited Local and General Adverse Reactions (%) Occurring within 4 Days of Vaccinationa with Separate Concomitant Administration of INFANRIX, ENGERIX-B, IPV, Haemophilus b (Hib) Conjugate Vaccine, and Pneumococcal Conjugate Vaccine (PCV7) (Modified Intent-to-Treat Cohort)
Adverse Reaction | INFANRIX, ENGERIX-B, IPV, Hib Vaccine, & PCV7
Adverse Reaction | Dose 1 | Dose 2 | Dose 3
Localb
n | 335 | 323 | 315
Pain, any | 32 | 30 | 30
Pain, Grade 2 or 3 | 9 | 9 | 9
Pain, Grade 3 | 3 | 2 | 1
Redness, any | 18 | 33 | 39
Redness, >20 mm | 0 | 0 | 2
Swelling, any | 10 | 20 | 25
Swelling, >20 mm | 1 | 0 | 1
General
n | 333 | 321 | 311
Feverc (≥100.4°F) | 20 | 30 | 24
Feverc (>101.3°F) | 5 | 8 | 6
Feverc (>102.2°F) | 0 | 3 | 2
Feverc (>103.1°F) | 0 | 0 | 0
n | 335 | 323 | 315
Drowsiness, any | 54 | 48 | 38
Drowsiness, Grade 2 or 3 | 18 | 12 | 11
Drowsiness, Grade 3 | 4 | 1 | 2
Irritability/Fussiness, any | 62 | 62 | 57
Irritability/Fussiness, Grade 2 or 3 | 19 | 21 | 19
Irritability/Fussiness, Grade 3 | 4 | 3 | 3
Loss of appetite, any | 28 | 27 | 24
Loss of appetite, Grade 2 or 3 | 5 | 3 | 5
Loss of appetite, Grade 3 | 1 | 0 | 0
Hib conjugate vaccine and PCV7 manufactured by Wyeth Pharmaceuticals Inc. IPV manufactured by Sanofi Pasteur SA.
Modified intent-to-treat cohort = All vaccinated subjects for whom safety data were available.
n = Number of infants for whom at least one symptom sheet was completed; for fever; numbers exclude missing temperature recordings or tympanic measurements.
Grade 2: Pain defined as cried/protested on touch; drowsiness defined as interfered with normal daily activities; irritability/fussiness defined as crying more than usual/interfered with normal daily activities; loss of appetite defined as eating less than usual/interfered with normal daily activities.
Grade 3: Pain defined as cried when limb was moved/spontaneously painful; drowsiness defined as prevented normal daily activities; irritability/fussiness defined as crying that could not be comforted/prevented normal daily activities; loss of appetite defined as no eating at all.
a Within 4 days of vaccination defined as day of vaccination and the next 3 days.
b Local reactions at the injection site for INFANRIX.
c Axillary temperatures increased by 1°C and oral temperatures increased by 0.5°C to derive equivalent rectal temperature.

In a U.S. study, the safety of a booster dose of INFANRIX was evaluated in children aged 15 to 18 months whose previous 3 DTaP doses were with INFANRIX (n = 251) or PEDIARIX (n = 559). Vaccines administered concurrently with the fourth dose of INFANRIX included measles, mumps, and rubella (MMR) vaccine (Merck & Co., Inc.), varicella vaccine (Merck & Co., Inc.), pneumococcal 7-valent conjugate (PCV7) vaccine (Wyeth Pharmaceuticals Inc.), and any U.S.-licensed Hib conjugate vaccine; these were given concomitantly in 13.2%, 6.3%, 37.4%, and 41.2% of subjects, respectively. Data on solicited adverse reactions were collected by parents using standardized diary cards for 4 consecutive days following each vaccine dose (i.e., day of vaccination and the next 3 days) (Table 2). Among subjects, 85% were White, 6% were Hispanic, 6% were Black, 1% were Asian, and 2% were of other racial/ethnic groups.

Table 2. Solicited Local and General Adverse Reactions (%) Occurring within 4 Days of Vaccinationa with INFANRIX Administered as the Fourth Dose following 3 Previous Doses of INFANRIX or PEDIARIX (Total Vaccinated Cohort)
Adverse Reaction | Group Primed with INFANRIXb; n = 247 | Group Primed with PEDIARIXc; n = 553
Locald
Pain, any | 45 | 48
Pain, Grade 2 or 3 | 19 | 19
Pain, Grade 3 | 4 | 3
Redness, any | 48 | 50
Redness, >20 mm | 6 | 6
Swelling, any | 33 | 33
Swelling, >20 mm | 4 | 5
Increase in mid-thigh circumference, any | 33 | 26
Increase in mid-thigh circumference, >40 mm | 0 | 1
General
Fevere (>99.5°F) | 9 | 15
Fevere (>100.4°F) | 5 | 7
Fevere (>101.3°F) | 2 | 2
Drowsiness, any | 36 | 31
Drowsiness, Grade 2 or 3 | 9 | 7
Drowsiness, Grade 3 | 2 | 1
Irritability, any | 52 | 54
Irritability, Grade 2 or 3 | 18 | 20
Irritability, Grade 3 | 3 | 1
Loss of appetite, any | 25 | 23
Loss of appetite, Grade 2 or 3 | 5 | 5
Loss of appetite, Grade 3 | 2 | 0
Total Vaccinated Cohort = All subjects who received a dose of study vaccine.
n = Number of subjects for whom at least one symptom sheet was completed.
Grade 2: Pain defined as cried/protested on touch; drowsiness defined as interfered with normal daily activities; irritability defined as crying more than usual/interfered with normal daily activities; loss of appetite defined as eating less than usual/no effect on normal daily activities.
Grade 3: Pain defined as cried when limb was moved/spontaneously painful; drowsiness defined as prevented normal daily activities; irritability defined as crying that could not be comforted/prevented normal daily activities; loss of appetite defined as eating less than usual/interfered with normal daily activities.
a Within 4 days of vaccination defined as day of vaccination and the next 3 days.
b Received INFANRIX, ENGERIX-B, IPV (Sanofi Pasteur SA), PCV7 vaccine (Wyeth Pharmaceuticals Inc.), and Hib conjugate vaccine (Wyeth Pharmaceuticals Inc.; no longer licensed in the United States) at 2, 4, and 6 months of age.
c Received PEDIARIX, PCV7 vaccine (Wyeth Pharmaceuticals Inc.), and Hib conjugate vaccine (Wyeth Pharmaceuticals Inc.; no longer licensed in the United States) at 2, 4, and 6 months of age or PCV7 vaccine 2 weeks later.
d Local reactions at the injection site for INFANRIX.
e Axillary temperatures.

In a U.S. study, the safety of a fifth consecutive dose of INFANRIX coadministered at separate sites with a fourth dose of IPV (Sanofi Pasteur SA) and a second dose of MMR vaccine (Merck & Co., Inc.) was evaluated in 1,053 children aged 4 to 6 years. Data on solicited adverse reactions were collected by parents using standardized diary cards for 4 consecutive days following each vaccine dose (i.e., day of vaccination and the next 3 days) (Table 3). Among subjects, 43% were White, 18% Hispanic, 15% Asian, 7% Black, and 17% were of other racial/ethnic groups.

Table 3. Solicited Local and General Adverse Reactions (%) Occurring within 4 Days of Vaccinationa with a Fifth Consecutive Dose of INFANRIX when Coadministered with IPV and MMR Vaccine (Total Vaccinated Cohort)
Localb | n = 1,039-1,043
Pain, any | 53
Pain, Grade 2 or 3c | 12
Pain, Grade 3c | 1
Redness, any | 37
Redness, ≥50 mm | 20
Redness, ≥110 mm | 4
Arm circumference increase, any | 38
Arm circumference increase, >20 mm | 7
Arm circumference increase, >30 mm | 3
Swelling, any | 27
Swelling, ≥50 mm | 12
Swelling, ≥110 mm | 2
General | n = 993-1,036
Drowsiness, any | 18
Drowsiness, Grade 3d | 1
Fever, ≥99.5°F | 15
Fever, >100.4°F | 4
Fever, >102.2°F | 1
Fever, >104°F | 0
Loss of appetite, any | 16
Loss of appetite, Grade 3e | 1
IPV manufactured by Sanofi Pasteur SA. MMR vaccine manufactured by Merck & Co., Inc.
Total Vaccinated Cohort = All vaccinated subjects for whom safety data were available.
n = Number of children with evaluable data for the reactions listed.
a Within 4 days of vaccination defined as day of vaccination and the next 3 days.
b Local reactions at the injection site for INFANRIX.
c Grade 2 defined as painful when the limb was moved; Grade 3 defined as preventing normal daily activities.
d Grade 3 defined as preventing normal daily activities.
e Grade 3 defined as not eating at all.

In the U.S. booster immunization studies in which INFANRIX was administered as the fourth or fifth dose in the DTaP series following previous doses with INFANRIX or PEDIARIX, large swelling reactions of the limb injected with INFANRIX were assessed.

In the fourth-dose study, a large swelling reaction was defined as injection site swelling with a diameter of >50 mm, a >50 mm increase in the mid-thigh circumference compared with the pre-vaccination measurement, and/or any diffuse swelling that interfered with or prevented daily activities. The overall incidence of large swelling reactions occurring within 4 days (Day 0-Day 3) following INFANRIX was 2.3%.

In the fifth-dose study, a large swelling reaction was defined as swelling that involved >50% of the injected upper arm length and that was associated with a >30 mm increase in mid-upper arm circumference within 4 days following vaccination. The incidence of large swelling reactions following the fifth consecutive dose of INFANRIX was 1.0%.

Less Common and Serious General Adverse Reactions

Selected adverse reactions reported from a double-blind, randomized Italian clinical efficacy trial involving 4,696 children administered INFANRIX or 4,678 children administered whole-cell DTP vaccine (DTwP) (manufactured by Connaught Laboratories, Inc.) as a 3-dose primary series are shown in Table 4. The incidence of rectal temperature ≥104°F, hypotonic-hyporesponsive episodes, and persistent crying ≥3 hours following administration of INFANRIX was significantly less than that following administration of whole-cell DTP vaccine.

Table 4. Selected Adverse Reactions Occurring within 48 Hours following Vaccination with INFANRIX or Whole-Cell DTP in Italian Infants at 2, 4, or 6 Months of Age
Reaction | INFANRIX; (n = 13,761 Doses) |  | Whole-Cell DTP Vaccine; (n = 13,520 Doses)
Reaction | Number | Rate/1,000 Doses | Number | Rate/1,000 Doses
Fever (≥104°F)a,b | 5 | 0.36 | 32 | 2.4
Hypotonic-hyporesponsive episodec | 0 | 0 | 9 | 0.67
Persistent crying ≥3 hoursa | 6 | 0.44 | 54 | 4.0
Seizuresd | 1e | 0.07 | 3f | 0.22
a P <0.001.
b Rectal temperatures.
c P = 0.002.
d Not statistically significant at P <0.05.
e Maximum rectal temperature within 72 hours of vaccination = 103.1°F.
f Maximum rectal temperature within 72 hours of vaccination = 99.5°F, 101.3°F, and 102.2°F.

In a German safety study that enrolled 22,505 infants (66,867 doses of INFANRIX administered as a 3-dose primary series at 3, 4, and 5 months of age), all subjects were monitored for unsolicited adverse events that occurred within 28 days following vaccination using report cards. In a subset of subjects (n = 2,457), these cards were standardized diaries which solicited specific adverse reactions that occurred within 8 days of each vaccination in addition to unsolicited adverse events which occurred from enrollment until approximately 30 days following the third vaccination. Cards from the whole cohort were returned at subsequent visits and were supplemented by spontaneous reporting by parents and a medical history after the first and second doses of vaccine. In the subset of 2,457, adverse events following the third dose of vaccine were reported via standardized diaries and spontaneous reporting at a follow-up visit. Adverse events in the remainder of the cohort were reported via report cards which were returned by mail approximately 28 days after the third dose of vaccine. Adverse reactions (rates per 1,000 doses) occurring within 7 days following any of the first 3 doses included: unusual crying (0.09), febrile seizure (0.0), afebrile seizure (0.13), and hypotonic-hyporesponsive episodes (0.01).

6.2 Postmarketing Experience

In addition to reports in clinical trials for INFANRIX, the following adverse reactions have been identified during postapproval use of INFANRIX. Because these reactions are reported voluntarily from a population of uncertain size, it is not always possible to reliably estimate their frequency or establish a causal relationship to vaccination.

Infections and Infestations

Bronchitis, cellulitis, respiratory tract infection.

Blood and Lymphatic System Disorders

Lymphadenopathy, thrombocytopenia.

Immune System Disorders

Anaphylactic reaction, hypersensitivity.

Nervous System Disorders

Encephalopathy, headache, hypotonia, syncope.

Ear and Labyrinth Disorders

Ear pain.

Cardiac Disorders

Cyanosis.

Respiratory, Thoracic, and Mediastinal Disorders

Apnea, cough.

Skin and Subcutaneous Tissue Disorders

Angioedema, erythema, pruritus, rash, urticaria.

General Disorders and Administration Site Conditions

Fatigue, injection site induration, injection site reaction, Sudden Infant Death Syndrome.

7 DRUG INTERACTIONS

7.1 Concomitant Vaccine Administration

In clinical trials, INFANRIX was given concomitantly with Hib conjugate vaccine, pneumococcal 7-valent conjugate vaccine, hepatitis B vaccine, IPV, and the second dose of MMR vaccine [see Adverse Reactions (6.1), Clinical Studies (14.3)].

When INFANRIX is administered concomitantly with other injectable vaccines, they should be given with separate syringes. INFANRIX should not be mixed with any other vaccine in the same syringe.

7.2 Immunosuppressive Therapies

Immunosuppressive therapies, including irradiation, antimetabolites, alkylating agents, cytotoxic drugs, and corticosteroids (used in greater than physiologic doses), may reduce the immune response to INFANRIX.

8 USE IN SPECIFIC POPULATIONS

8.4 Pediatric Use

Safety and effectiveness of INFANRIX in infants aged younger than 6 weeks and children aged 7 to 16 years have not been established. INFANRIX is not approved for use in these age groups.

11 DESCRIPTION

INFANRIX (Diphtheria and Tetanus Toxoids and Acellular Pertussis Vaccine Adsorbed) is a noninfectious, sterile vaccine for intramuscular administration. Each 0.5-mL dose is formulated to contain 25 Lf of diphtheria toxoid, 10 Lf of tetanus toxoid, 25 mcg of inactivated pertussis toxin (PT), 25 mcg of filamentous hemagglutinin (FHA), and 8 mcg of pertactin (69 kiloDalton outer membrane protein).

The diphtheria toxin is produced by growing Corynebacterium diphtheriae (C. diphtheriae) in Fenton medium containing a bovine extract. Tetanus toxin is produced by growing Clostridium tetani (C. tetani) in a modified Latham medium derived from bovine casein. The bovine materials used in these extracts are sourced from countries which the United States Department of Agriculture (USDA) has determined neither have nor present an undue risk for bovine spongiform encephalopathy (BSE). Both toxins are detoxified with formaldehyde, concentrated by ultrafiltration, and purified by precipitation, dialysis, and sterile filtration.

The acellular pertussis antigens (PT, FHA, and pertactin) are isolated from Bordetella pertussis (B. pertussis) culture grown in modified Stainer-Scholte liquid medium. PT and FHA are isolated from the fermentation broth; pertactin is extracted from the cells by heat treatment and flocculation. The antigens are purified in successive chromatographic and precipitation steps. PT is detoxified using glutaraldehyde and formaldehyde. FHA and pertactin are treated with formaldehyde.

Diphtheria and tetanus toxoids and pertussis antigens (PT, FHA, and pertactin) are individually adsorbed onto aluminum hydroxide.

Diphtheria and tetanus toxoid potency is determined by measuring the amount of neutralizing antitoxin in previously immunized guinea pigs. The potency of the acellular pertussis components (PT, FHA, and pertactin) is determined by enzyme-linked immunosorbent assay (ELISA) on sera from previously immunized mice.

Each 0.5-mL dose contains aluminum hydroxide as adjuvant (formulated to contain 0.5 mg aluminum) and 4.4 mg of sodium chloride. The aluminum content is measured by assay. Each dose also contains ≤100 mcg of residual formaldehyde and ≤100 mcg of polysorbate 80 (Tween 80).

The tip cap and rubber plunger stopper of the prefilled syringe are not made with natural rubber latex.

INFANRIX is formulated without preservatives.

12 CLINICAL PHARMACOLOGY

12.1 Mechanism of Action

Diphtheria

Diphtheria is an acute toxin-mediated infectious disease caused by toxigenic strains of C. diphtheriae. Protection against disease is due to the development of neutralizing antibodies to the diphtheria toxin. A serum diphtheria antitoxin level of 0.01 IU/mL is the lowest level giving some degree of protection; a level of 0.1 IU/mL is regarded as protective.^1

Tetanus

Tetanus is an acute toxin-mediated infectious disease caused by a potent exotoxin released by C. tetani. Protection against disease is due to the development of neutralizing antibodies to the tetanus toxin. A serum tetanus antitoxin level of at least 0.01 IU/mL, measured by neutralization assays, is considered the minimum protective level.^2,3 A level of 0.1 IU/mL is considered protective.^4

Pertussis

Pertussis (whooping cough) is a disease of the respiratory tract caused by B. pertussis. The role of the different components produced by B. pertussis in either the pathogenesis of, or the immunity to, pertussis is not well understood. There is no well-established serological correlate of protection for pertussis.

13 NONCLINICAL TOXICOLOGY

13.1 Carcinogenesis, Mutagenesis, Impairment of Fertility

INFANRIX has not been evaluated for carcinogenic or mutagenic potential or for impairment of fertility.

14 CLINICAL STUDIES

14.1 Diphtheria and Tetanus

Efficacy of diphtheria toxoid used in INFANRIX was determined on the basis of immunogenicity studies. A VERO cell toxin-neutralizing test confirmed the ability of infant sera (N = 45), obtained one month after a 3-dose primary series, to neutralize diphtheria toxin. Levels of diphtheria antitoxin ≥0.01 IU/mL were achieved in 100% of the sera tested.

Efficacy of tetanus toxoid used in INFANRIX was determined on the basis of immunogenicity studies. An in vivo mouse neutralization assay confirmed the ability of infant sera (N = 45), obtained 1 month after a 3-dose primary series, to neutralize tetanus toxin. Levels of tetanus antitoxin ≥0.01 IU/mL were achieved in 100% of the sera tested.

14.2 Pertussis

Efficacy of a 3-dose primary series of INFANRIX has been assessed in 2 clinical studies.

A double-blind, randomized, active Diphtheria and Tetanus Toxoids (DT)-controlled trial conducted in Italy assessed the absolute protective efficacy of INFANRIX when administered at 2, 4, and 6 months of age. The population used in the primary analysis of the efficacy of INFANRIX included 4,481 infants vaccinated with INFANRIX and 1,470 DT vaccinees. The mean length of follow-up was 17 months, beginning 30 days after the third dose of vaccine. After 3 doses, the absolute protective efficacy of INFANRIX against WHO-defined typical pertussis (21 days or more of paroxysmal cough with infection confirmed by culture and/or serologic testing) was 84% (95% CI: 76, 89). When the definition of pertussis was expanded to include clinically milder disease with respect to type and duration of cough, with infection confirmed by culture and/or serologic testing, the efficacy of INFANRIX was calculated to be 71% (95% CI: 60, 78) against >7 days of any cough and 73% (95% CI: 63, 80) against ≥14 days of any cough. Vaccine efficacy after 3 doses and with no booster dose in the second year of life was assessed in 2 subsequent follow-up periods. A follow-up period from 24 months to a mean age of 33 months was conducted in a partially unblinded cohort (children who received DT were offered pertussis vaccine and those who declined were retained in the study cohort). During this period, the efficacy of INFANRIX against WHO-defined pertussis was 78% (95% CI: 62, 87). During the third follow-up period, which was conducted in an unblinded manner among children aged 3 to 6 years, the efficacy of INFANRIX against WHO-defined pertussis was 86% (95% CI: 79, 91). Thus, protection against pertussis in children administered 3 doses of INFANRIX in infancy was sustained to 6 years of age.

A prospective efficacy trial was also conducted in Germany employing a household contact study design. In preparation for this study, 3 doses of INFANRIX were administered at 3, 4, and 5 months of age to more than 22,000 children living in 6 areas of Germany in a safety and immunogenicity study. Infants who did not participate in the safety and immunogenicity study could have received a DTwP vaccine or DT vaccine. Index cases were identified by spontaneous presentation to a physician. Households with at least one other member (i.e., besides index case) aged 6 through 47 months were enrolled. Household contacts of index cases were monitored for incidence of pertussis by a physician who was blinded to the vaccination status of the household. Calculation of vaccine efficacy was based on attack rates of pertussis in household contacts classified by vaccination status. Of the 173 household contacts who had not received a pertussis vaccine, 96 developed WHO-defined pertussis, as compared with 7 of 112 contacts vaccinated with INFANRIX. The protective efficacy of INFANRIX was calculated to be 89% (95% CI: 77, 95), with no indication of waning of protection up until the time of the booster vaccination. The average age of infants vaccinated with INFANRIX at the end of follow-up in this trial was 13 months (range: 6 to 25 months). When the definition of pertussis was expanded to include clinically milder disease, with infection confirmed by culture and/or serologic testing, the efficacy of INFANRIX against ≥7 days of any cough was 67% (95% CI: 52, 78) and against ≥7 days of paroxysmal cough was 81% (95% CI: 68, 89). The corresponding efficacy of INFANRIX against ≥14 days of any cough or paroxysmal cough were 73% (95% CI: 59, 82) and 84% (95% CI: 71, 91), respectively.

Pertussis Immune Response to INFANRIX Administered as a 3-Dose Primary Series

The immune responses to each of the 3 pertussis antigens contained in INFANRIX were evaluated in sera obtained 1 month after the third dose of vaccine in each of 3 studies (schedule of administration: 2, 4, and 6 months of age in the Italian efficacy study and one U.S. study; 3, 4, and 5 months of age in the German efficacy study). One month after the third dose of INFANRIX, the response rates to each pertussis antigen were similar in all 3 studies. Thus, although a serologic correlate of protection for pertussis has not been established, the antibody responses to these 3 pertussis antigens (PT, FHA, and pertactin) in a U.S. population were similar to those achieved in 2 populations in which efficacy of INFANRIX was demonstrated.

14.3 Immune Response to Concomitantly Administered Vaccines

In a U.S. study, INFANRIX was given concomitantly, at separate sites, with Hib conjugate vaccine (Sanofi Pasteur SA) at 2, 4, and 6 months of age. Subjects also received ENGERIX-B and oral poliovirus vaccine (OPV). One month after the third dose of Hib conjugate vaccine, 90% of 72 infants had anti-PRP (polyribosyl-ribitol-phosphate) ≥1.0 mcg/mL.

In a U.S. study, INFANRIX was given concomitantly, at separate sites, with ENGERIX-B, IPV (Sanofi Pasteur SA), pneumococcal 7-valent conjugate (PCV7), and Hib conjugate vaccines (Wyeth Pharmaceuticals Inc.; no longer licensed in the United States) at 2, 4, and 6 months of age. Immune responses were measured in sera obtained approximately 1 month after the third dose of vaccines. Among 121 subjects who had not received a birth dose of hepatitis B vaccine, 99.2% had anti-HBsAg (hepatitis B surface antigen) ≥10 mIU/mL following the third dose of ENGERIX-B. Among 153 subjects, 100% had anti-poliovirus 1, 2, and 3, ≥1:8 following the third dose of IPV. Although serological correlates for protection have not been established for the pneumococcal serotypes, a threshold level of ≥0.3 mcg/mL was evaluated. Following the third dose of PCV7 vaccine, 91.8% to 99.4% of subjects (n = 146-156) had anti-pneumococcal polysaccharide ≥0.3 mcg/mL for serotypes 4, 9V, 14, 18C, 19F, and 23F, and 73.0% had a level ≥0.3 mcg/mL for serotype 6B.

15 REFERENCES

1. Vitek CR and Wharton M. Diphtheria Toxoid. In: Plotkin SA, Orenstein WA, and Offit PA, eds. Vaccines. 5th ed. Saunders; 2008:139-156.
2. Wassilak SGF, Roper MH, Kretsinger K, and Orenstein WA. Tetanus Toxoid. In: Plotkin SA, Orenstein WA, and Offit PA, eds. Vaccines. 5th ed. Saunders; 2008:805-839.
3. Department of Health and Human Services, Food and Drug Administration. Biological products; Bacterial vaccines and toxoids; Implementation of efficacy review; Proposed rule. Federal Register. December 13, 1985;50(240):51002-51117.
4. Centers for Disease Control and Prevention. General Recommendations on Immunization. Recommendations of the Advisory Committee on Immunization Practices (ACIP). MMWR. 2006;55(RR-15):1-48.

16 HOW SUPPLIED/STORAGE AND HANDLING

INFANRIX is available in 0.5-mL single-dose, disposable, prefilled TIP‑LOK syringes (Luer Lock syringes) packaged without needles. TIP-LOK syringes are to be used with Luer Lock compatible needles. The tip cap and rubber plunger stopper of the prefilled syringe are not made with natural rubber latex.

NDC 58160-810-43 Syringe in Package of 10: NDC 58160-810-52

Store refrigerated between 2° and 8°C (36° and 46°F). Do not freeze. Discard if the vaccine has been frozen.

17 PATIENT COUNSELING INFORMATION

Provide the following information to the parent or guardian:

- Inform of the potential benefits and risks of immunization with INFANRIX, and of the importance of completing the immunization series.
- Inform about the potential for adverse reactions that have been temporally associated with administration of INFANRIX or other vaccines containing similar components.
- Instruct to report any adverse events to their healthcare provider.
- Give the Vaccine Information Statements, which are required by the National Childhood Vaccine Injury Act of 1986 to be given prior to immunization. These materials are available free of charge at the Centers for Disease Control and Prevention (CDC) website (www.cdc.gov/vaccines).

ENGERIX-B, INFANRIX, PEDIARIX, and TIP-LOK are trademarks owned by or licensed to the GSK group of companies.

Manufactured by GlaxoSmithKline Biologicals

Rixensart, Belgium, U.S. License 1617

GSK Vaccines GmbH

Marburg, Germany, U.S. License 1617

Distributed by GlaxoSmithKline

Durham, NC 27701

©2024 GSK group of companies or its licensor.

INF:33PI

PACKAGE LABEL

PRINCIPAL DISPLAY PANEL

NDC 58160-810-52

INFANRIX

Diphtheria and Tetanus Toxoids and Acellular Pertussis Vaccine Adsorbed

DTaP

Rx only

For Use from 6 Weeks to 6 Years of Age

10 Disposable Single-Dose Prefilled TIP-LOK Syringes each containing one 0.5-mL dose

TIP-LOK syringes to be used with Luer-Lok compatible needles

NEEDLES NOT INCLUDED

GSK

Infanrix

INFANRIX and TIP-LOK are trademarks owned by or licensed to the GSK group of companies.

Made in Belgium

©2023 GSK group of companies or its licensor.

Rev. 12/23

518145